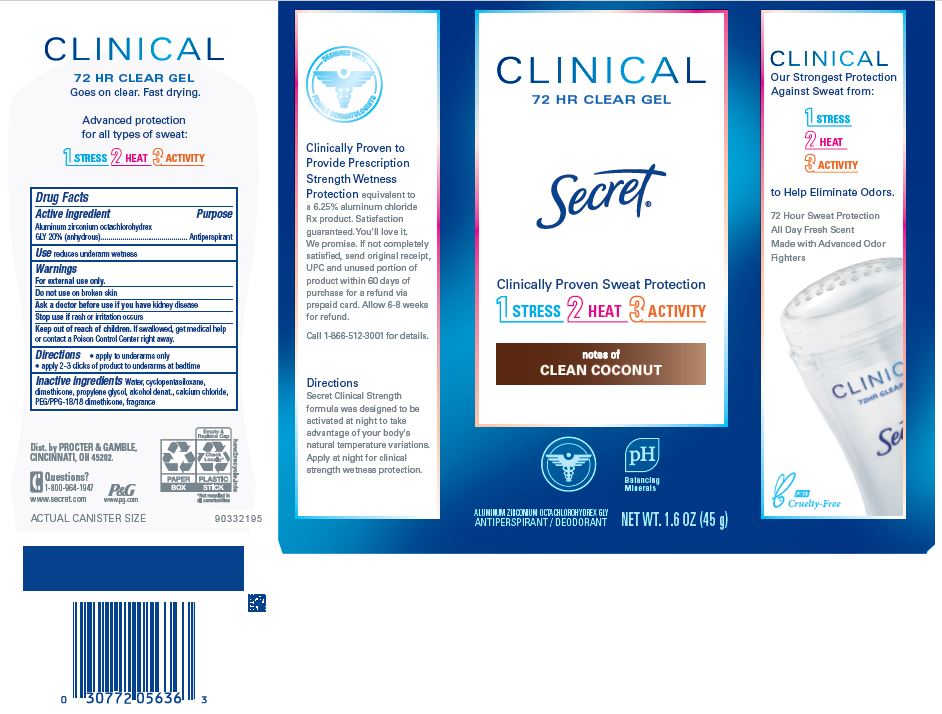 DRUG LABEL: Secret Clinical Clear Clean Coconut
NDC: 69423-687 | Form: GEL
Manufacturer: The Procter & Gamble Manufacturing Company
Category: otc | Type: HUMAN OTC DRUG LABEL
Date: 20251231

ACTIVE INGREDIENTS: ALUMINUM ZIRCONIUM OCTACHLOROHYDREX GLY 20 g/100 g
INACTIVE INGREDIENTS: PROPYLENE GLYCOL; WATER; DIMETHICONE; CALCIUM CHLORIDE; PEG/PPG-18/18 DIMETHICONE; CYCLOPENTASILOXANE; ALCOHOL

Secret Clincial Clear Clean Coconut

Drug Facts

Active ingredient

Aluminum zirconium octachlorohydrex Gly 20% (anhydrous)

Purpose

Antiperspirant

Use

reduces underarm wetness

Warnings

For external use only.

Do not use on broken skin

Ask a doctor before use if you have kidney disease

Stop use if rash or irritation occurs

Keep out of reach of children. If swallowed, get medical help or contact a Poison Control Center right away.

Directions

- apply to underarms only
- apply 2-3 clicks of product to underarms at bedtime

Inactive ingredients

Water, cyclopentasiloxane, dimethicone, propylene glycol, alcohol denat., calcium chloride, PEG/PPG-18/18 dimethicone, fragrance

Questions?

1-800-964-1947

www.secret.com

Dist. by PROCTER & GAMBLE,
CINCINNATI, OH 45202.

www.secret.com

PRINCIPAL DISPLAY PANEL - 45 g Carton

Secret®

CLINICAL

72 HR CLEAR GEL

NOTES OF CLEAN COCONUT

ALUMINUM ZIRCONIUM OCTACHLOROHYDREX GLY

ANTIPERSPIRANT / DEODORANT

NET WT. 1.6 OZ (45g)